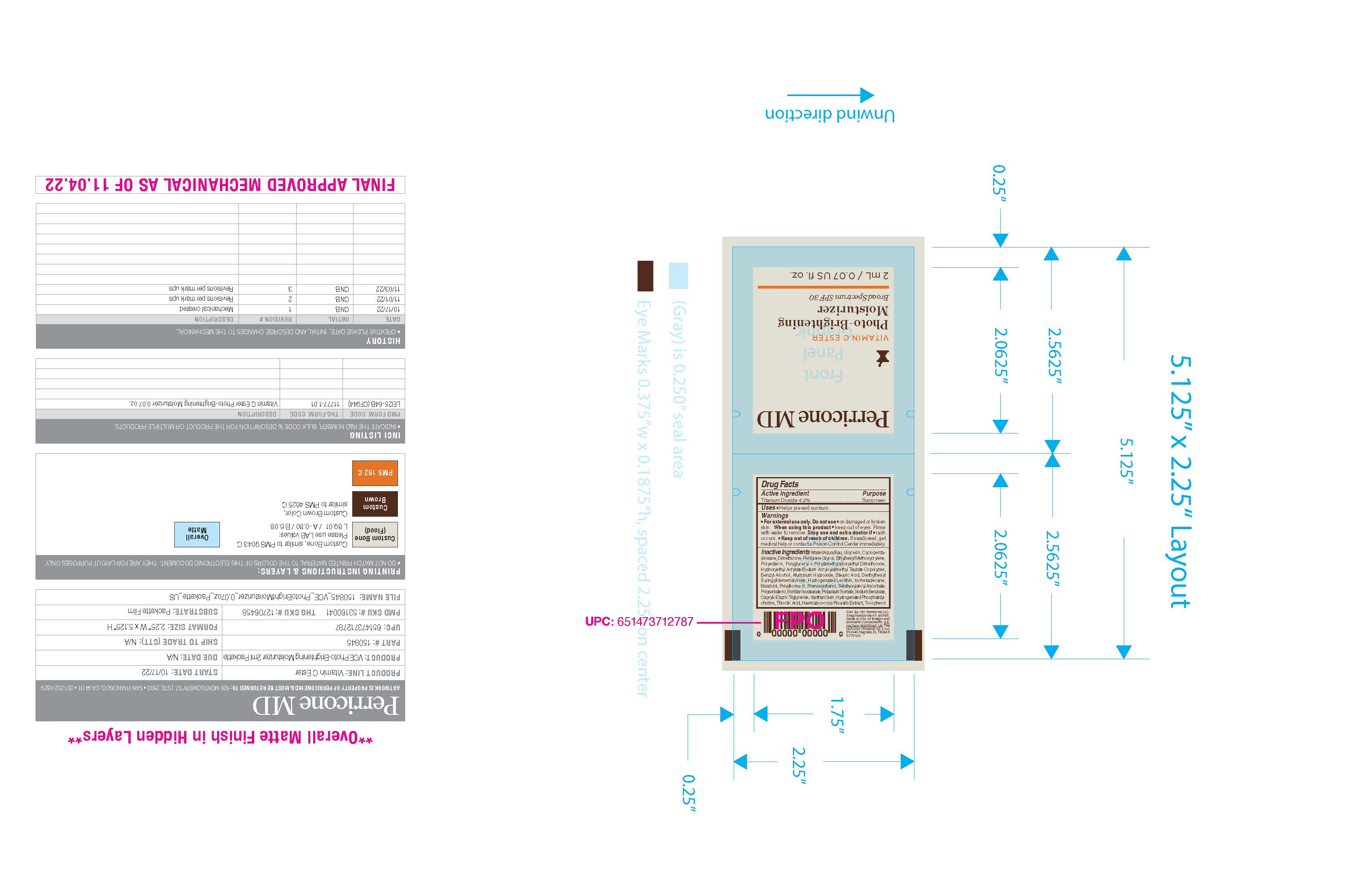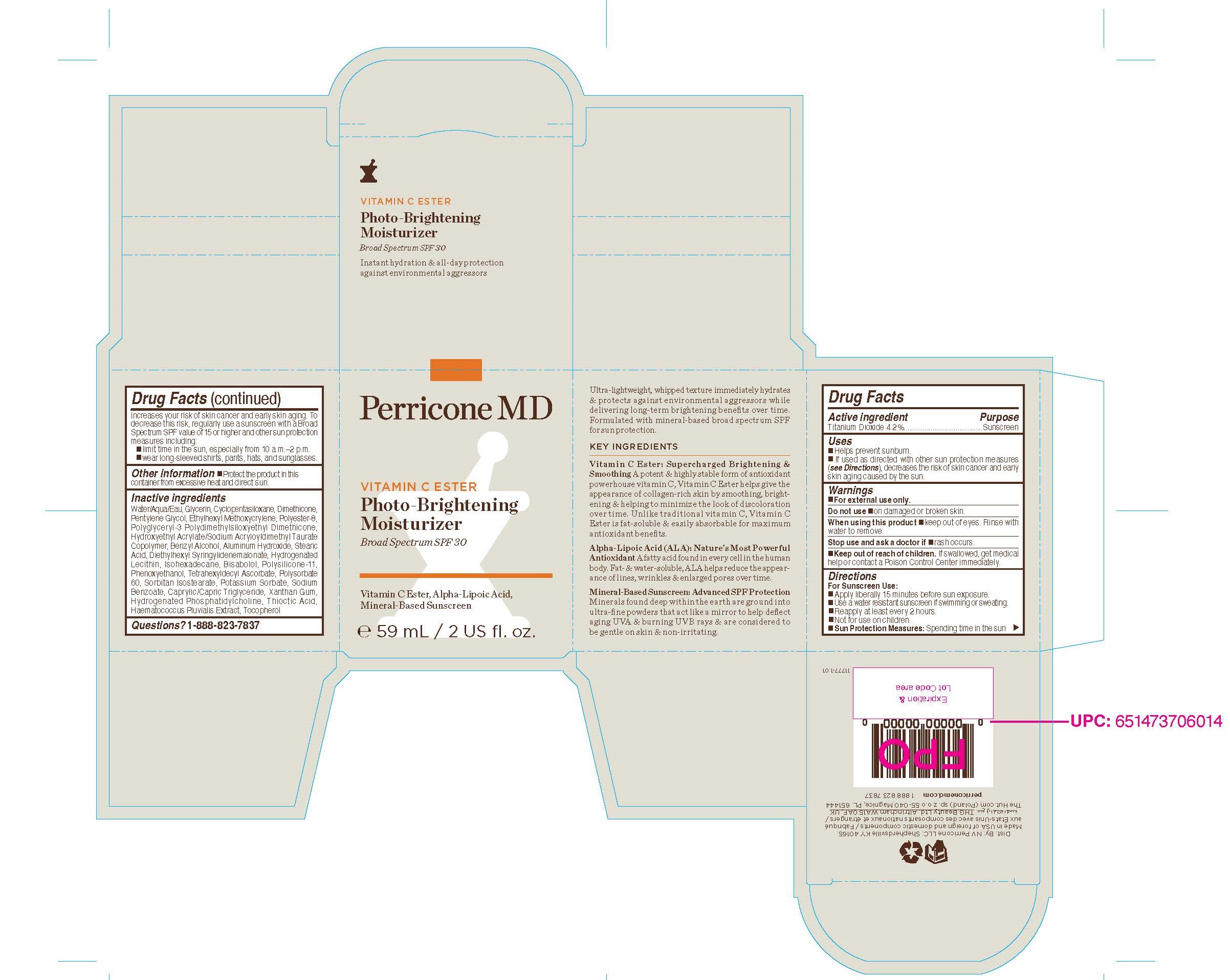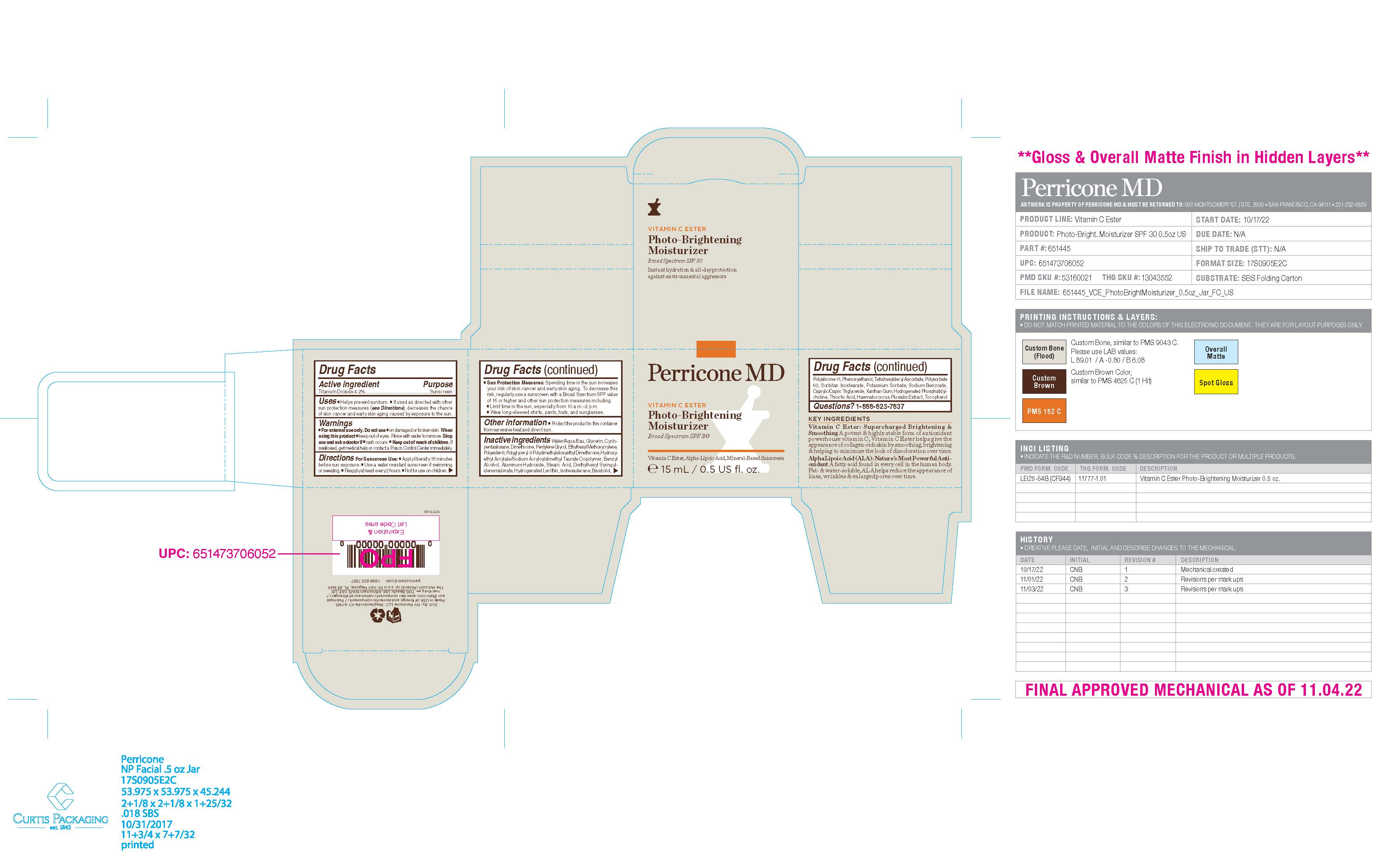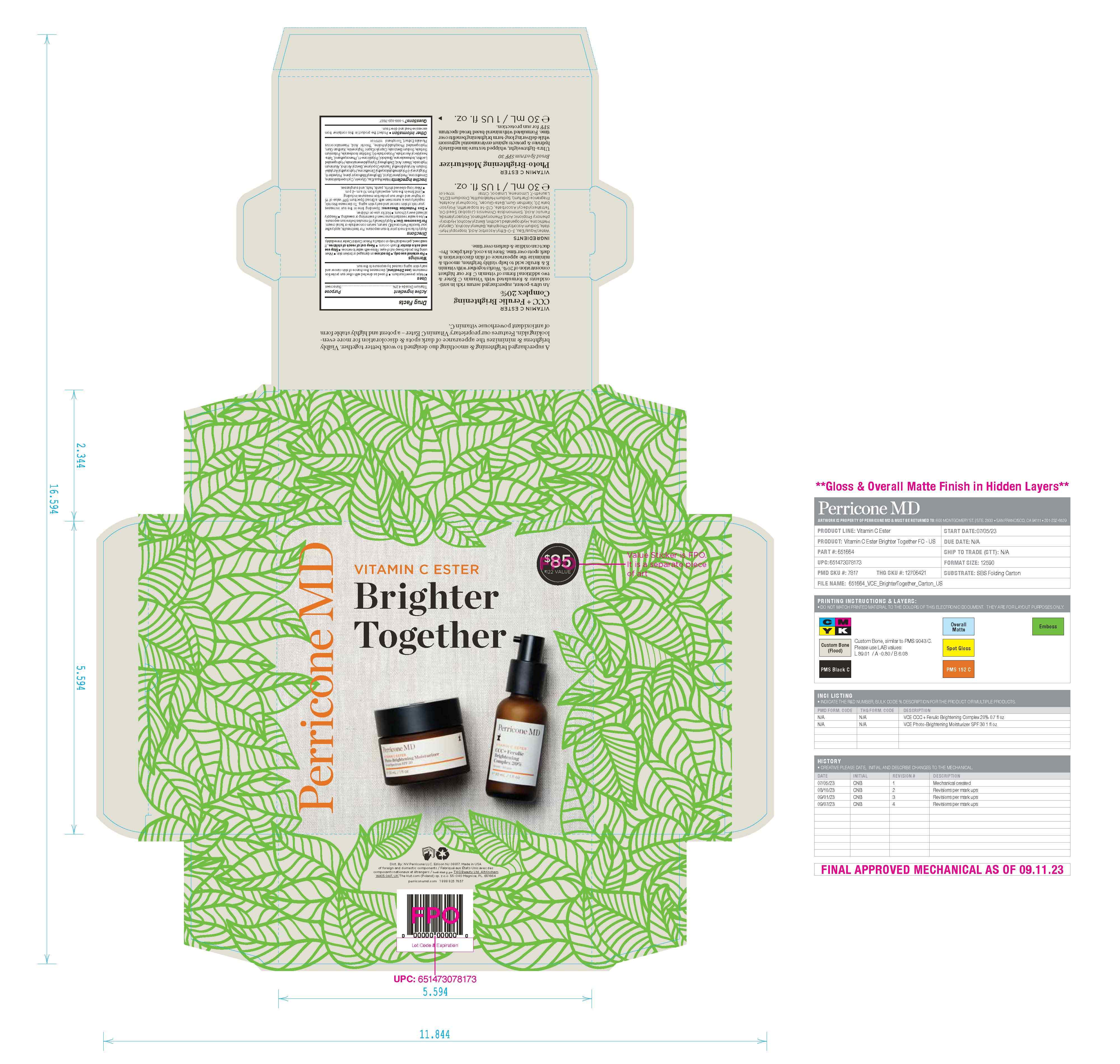 DRUG LABEL: PERRICONE MD VITAMIN C ESTER PHOTO-BRIGHTENING MOISTURIZER BROAD SPECTRUM SPF 30
NDC: 84448-643 | Form: CREAM
Manufacturer: THG Beauty USA LLC
Category: otc | Type: HUMAN OTC DRUG LABEL
Date: 20251023

ACTIVE INGREDIENTS: TITANIUM DIOXIDE 4.2 g/100 mL
INACTIVE INGREDIENTS: PHENOXYETHANOL; POLYSORBATE 60; HYDROGENATED SOYBEAN LECITHIN; DIMETHICONE/VINYL DIMETHICONE CROSSPOLYMER (SOFT PARTICLE); XANTHAN GUM; CYCLOPENTASILOXANE; PENTYLENE GLYCOL; BENZYL ALCOHOL; STEARIC ACID; ALUMINUM HYDROXIDE; ISOHEXADECANE; THIOCTIC ACID; DIETHYLHEXYL SYRINGYLIDENEMALONATE; POTASSIUM SORBATE; MEDIUM-CHAIN TRIGLYCERIDES; HAEMATOCOCCUS PLUVIALIS; TOCOPHEROL; POLYESTER-8 (1400 MW, CYANODIPHENYLPROPENOYL CAPPED); TETRAHEXYLDECYL ASCORBATE; SORBITAN ISOSTEARATE; HYDROXYETHYL ACRYLATE/SODIUM ACRYLOYLDIMETHYL TAURATE COPOLYMER (100000 MPA.S AT 1.5%); POLYGLYCERYL-3 POLYDIMETHYLSILOXYETHYL DIMETHICONE (4000 MPA.S); WATER; GLYCERIN; ETHYLHEXYL METHOXYCRYLENE; BISABOLOL; HYDROGENATED SOYBEAN PHOSPHATIDYLCHOLINE; DIMETHICONE; SODIUM BENZOATE

ACTIVE INGREDIENT

Titanium Dioxide 4.2%

PURPOSE

Sunscreen

INDICATIONS AND USAGE

■ Helps prevent sunburn.
■ If used as directed with other sun protection measures (see Directions), decreases the risk of skin cancer and early skin aging caused by the sun.

WARNINGS

■ For external use only.

DO NOT USE

■ on damaged or broken skin.

WHEN USING

■ keep out of eyes. Rinse with water to remove.

Stop use and ask a doctor if ■ rash occurs.

KEEP OUT OF REACH OF CHILDREN

If swallowed, get medical help or contact a Poison Control Center immediately.

DOSAGE AND ADMINISTRATION

For Sunscreen Use:
■ Apply liberally 15 minutes before sun exposure.
■ Use a water resistant sunscreen if swimming or sweating.
■ Reapply at least every 2 hours.
■ Not for use on children.
■ Sun Protection Measures: Spending time in the sun increases your risk of skin cancer and early skin aging. To decrease this risk, regularly use a sunscreen with a Broad Spectrum SPF value of 15 or higher and other sun protection measures including:
■ limit time in the sun, especially from 10 a.m.–2 p.m.
■ wear long-sleeved shirts, pants, hats, and sunglasses

OTHER SAFETY INFORMATION

Protect the product in this container from excessive heat and direct sun.

INACTIVE INGREDIENT

Water/Aqua/Eau, Glycerin, Cyclopentasiloxane, Dimethicone,
Pentylene Glycol, Ethylhexyl Methoxycrylene, Polyester-8,
Polyglyceryl-3 Polydimethylsiloxyethyl Dimethicone,
Hydroxyethyl Acrylate/Sodium Acryloyldimethyl Taurate
Copolymer, Benzyl Alcohol, Aluminum Hydroxide, Stearic
Acid, Diethylhexyl Syringylidenemalonate, Hydrogenated
Lecithin, Isohexadecane, Bisabolol, Polysilicone-11,
Phenoxyethanol, Tetrahexyldecyl Ascorbate, Polysorbate
60, Sorbitan Isostearate, Potassium Sorbate, Sodium
Benzoate, Caprylic/Capric Triglyceride, Xanthan Gum,
Hydrogenated Phosphatidylcholine, Thioctic Acid,
Haematococcus Pluvialis Extract, Tocopherol

QUESTIONS

1-888-823-7837